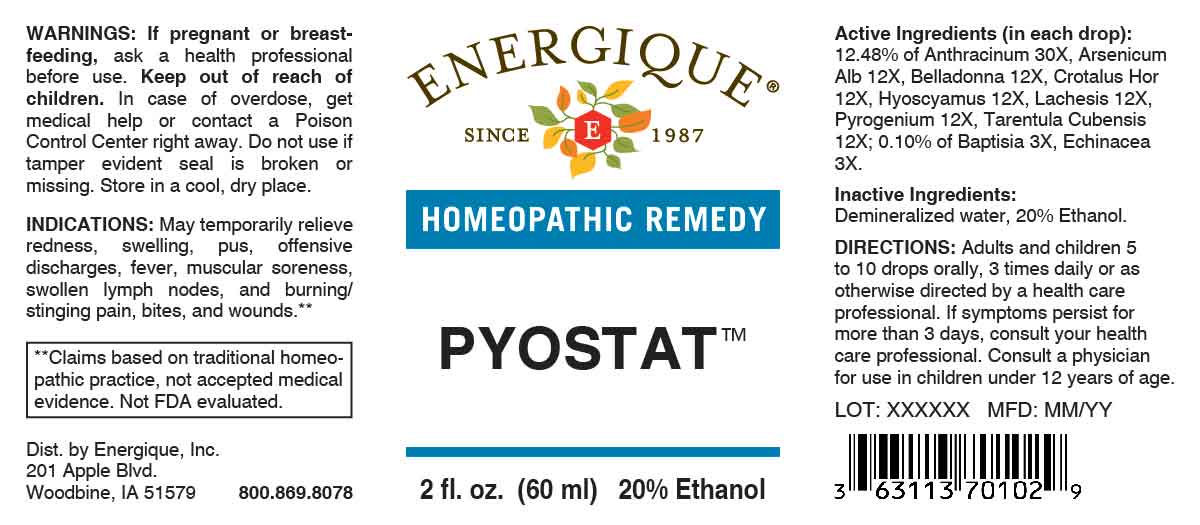 DRUG LABEL: Pyostat
NDC: 44911-0709 | Form: LIQUID
Manufacturer: Energique, Inc.
Category: homeopathic | Type: HUMAN OTC DRUG LABEL
Date: 20251006

ACTIVE INGREDIENTS: BAPTISIA TINCTORIA ROOT 3 [hp_X]/1 mL; ECHINACEA ANGUSTIFOLIA WHOLE 3 [hp_X]/1 mL; ARSENIC TRIOXIDE 12 [hp_X]/1 mL; ATROPA BELLADONNA 12 [hp_X]/1 mL; CROTALUS HORRIDUS HORRIDUS VENOM 12 [hp_X]/1 mL; HYOSCYAMUS NIGER 12 [hp_X]/1 mL; LACHESIS MUTA VENOM 12 [hp_X]/1 mL; RANCID BEEF 12 [hp_X]/1 mL; CITHARACANTHUS SPINICRUS 12 [hp_X]/1 mL; BACILLUS ANTHRACIS IMMUNOSERUM RABBIT 30 [hp_X]/1 mL
INACTIVE INGREDIENTS: WATER; ALCOHOL

DRUG FACTS:

ACTIVE INGREDIENTS:

(in each drop): 12.48% of Anthracinum 30X, Arsenicum Album 12X, Belladonna 12X, Crotalus Horridus 12X, Hyoscyamus Niger 12X, Lachesis Mutus 12X, Pyrogenium 12X, Tarentula Cubensis 12X; 0.10% of Baptisia Tinctoria 3X, Echinacea (Angustifolia) 3X.

PURPOSE:

May temporarily relieve redness, swelling, pus, offensive discharges, fever, muscular soreness, swollen lymph nodes, and burning/stinging pain, bites, and wounds.**

**Claims based on traditional homeopathic practice, not accepted medical evidence. Not FDA evaluated.

WARNINGS:

If pregnant or breastfeeding, ask a health professional before use.

Keep out of reach of children. In case of overdose, get medical help or contact a Poison Control Center right away.

Do not use if tamper evident seal is broken or missing.

Store in a cool, dry place.

KEEP OUT OF REACH OF CHILDREN:

In case of overdose, get medical help or contact a Poison Control Center right away.

DIRECTIONS:

Adults and children 5 to 10 drops orally, 3 times daily or as otherwise directed by a health care professional. If symptoms persist for more than 3 days, consult your health care professional. Consult a physician for use in children under 12 years of age.

INDICATIONS:

May temporarily relieve redness, swelling, pus, offensive discharges, fever, muscular soreness, swollen lymph nodes, and burning/stinging pain, bites, and wounds.**

**Claims based on traditional homeopathic practice, not accepted medical evidence. Not FDA evaluated.

INACTIVE INGREDIENTS:

Demineralized water, 20% Ethanol.

QUESTIONS:

Dist. by Energique, Inc.

201 Apple Blvd.
Woodbine, IA 51579

800.869.8078

PACKAGE LABEL DISPLAY:

ENERGIQUE
SINCE 1987
HOMEOPATHIC REMEDY
PYOSTAT
2 fl. oz. (60 ml)